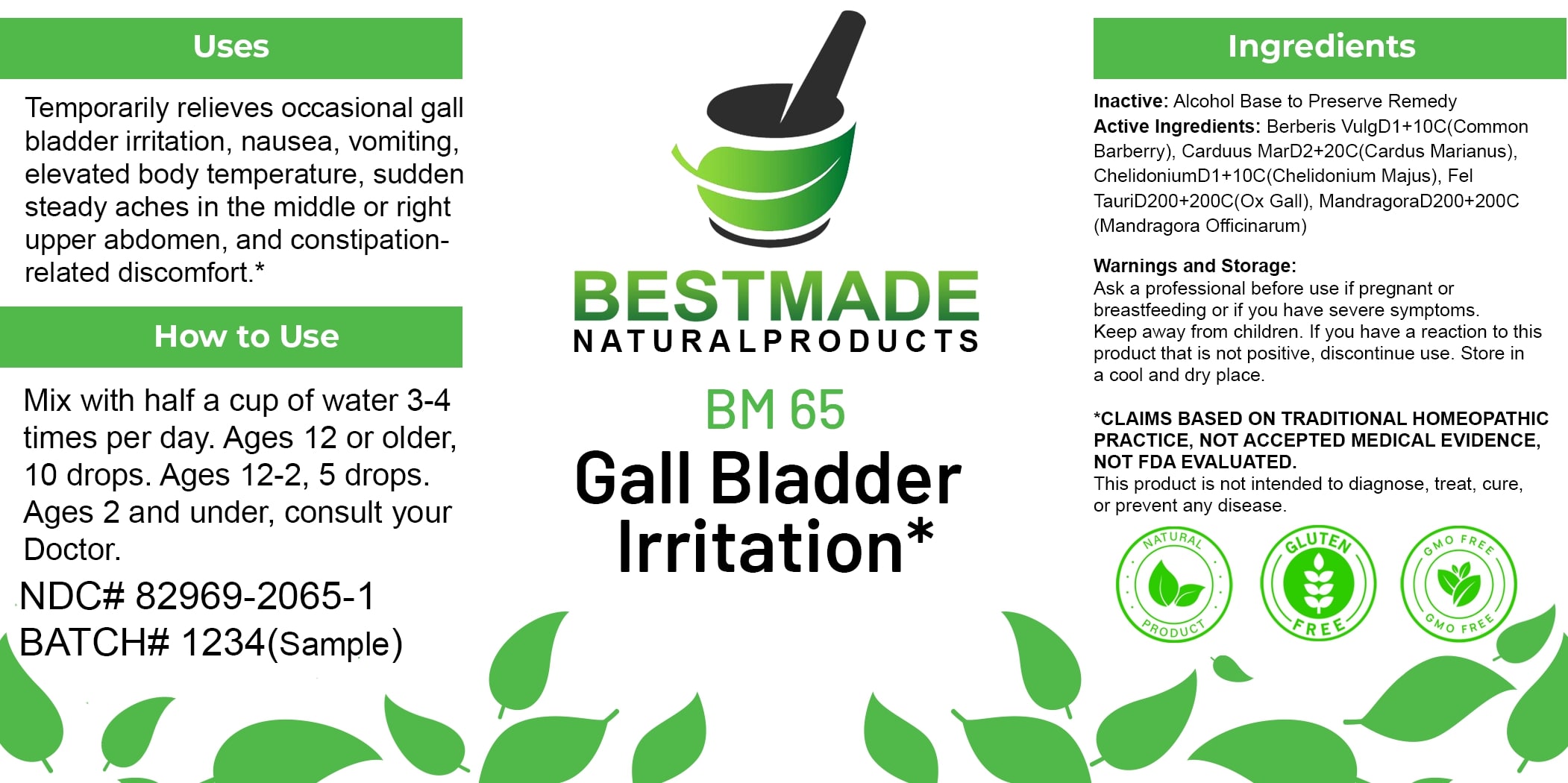 DRUG LABEL: Bestmade Natural Products BM65
NDC: 82969-2065 | Form: LIQUID
Manufacturer: Bestmade Natural Products
Category: homeopathic | Type: HUMAN OTC DRUG LABEL
Date: 20250130

ACTIVE INGREDIENTS: BOS TAURUS BILE 30 [hp_C]/30 [hp_C]; MANDRAGORA OFFICINARUM ROOT 30 [hp_C]/30 [hp_C]; CHELIDONIUM MAJUS 30 [hp_C]/30 [hp_C]; MILK THISTLE 30 [hp_C]/30 [hp_C]; BERBERIS VULGARIS ROOT BARK 30 [hp_C]/30 [hp_C]
INACTIVE INGREDIENTS: ALCOHOL 30 [hp_C]/30 [hp_C]

BM65

DOSAGE AND ADMINISTRATION

How to Use

Mix with half a cup of water 3-4 times per day. Ages 12 or older, 10 drops. Ages 12-2, 5 drops. Ages 2 and under, consult your Doctor.

INACTIVE INGREDIENT

Ingredients

Inactive: Alcohol Base to Preserve Remedy

ACTIVE INGREDIENT

Active Ingredients: Berberis VulgD1+10C(Common Barberry), Carduus MarD2+20C(Cardus Marianus), ChelidoniumD1+10C(Chelidonium Majus), Fel TauriD200+200C(Ox Gall), MandragoraD200+200C (Mandragora Officinarum)

Uses

Temporarily relieves occasional gall bladder irritation, nausea, vomiting, elevated body temperature, sudden steady aches in the middle or right upper abdomen, and constipation-related discomfort.*

*CLAIMS BASED ON TRADITIONAL HOMEOPATHIC PRACTICE, NOT ACCEPTED MEDICAL EVIDENCE, NOT FDA EVALUATED.

This product is not intended to diagnose, treat, cure, or prevent any disease.

Uses

Temporarily relieves occasional gall bladder irritation, nausea, vomiting, elevated body temperature, sudden steady aches in the middle or right upper abdomen, and constipation-related discomfort.*

*CLAIMS BASED ON TRADITIONAL HOMEOPATHIC PRACTICE, NOT ACCEPTED MEDICAL EVIDENCE, NOT FDA EVALUATED.

This product is not intended to diagnose, treat, cure, or prevent any disease.

KEEP OUT OF REACH OF CHILDREN

Warnings and Storage:

Ask a professional before use if pregnant or breastfeeding or if you have severe symptoms. Keep away from children. If you have a reaction to this product that is not positive, discontinue use. Store in a cool and dry place.

Warnings and Storage:

Ask a professional before use if pregnant or breastfeeding or if you have severe symptoms. Keep away from children. If you have a reaction to this product that is not positive, discontinue use. Store in a cool and dry place.

*CLAIMS BASED ON TRADITIONAL HOMEOPATHIC PRACTICE, NOT ACCEPTED MEDICAL EVIDENCE, NOT FDA EVALUATED.

This product is not intended to diagnose, treat, cure, or prevent any disease.

Entire package label